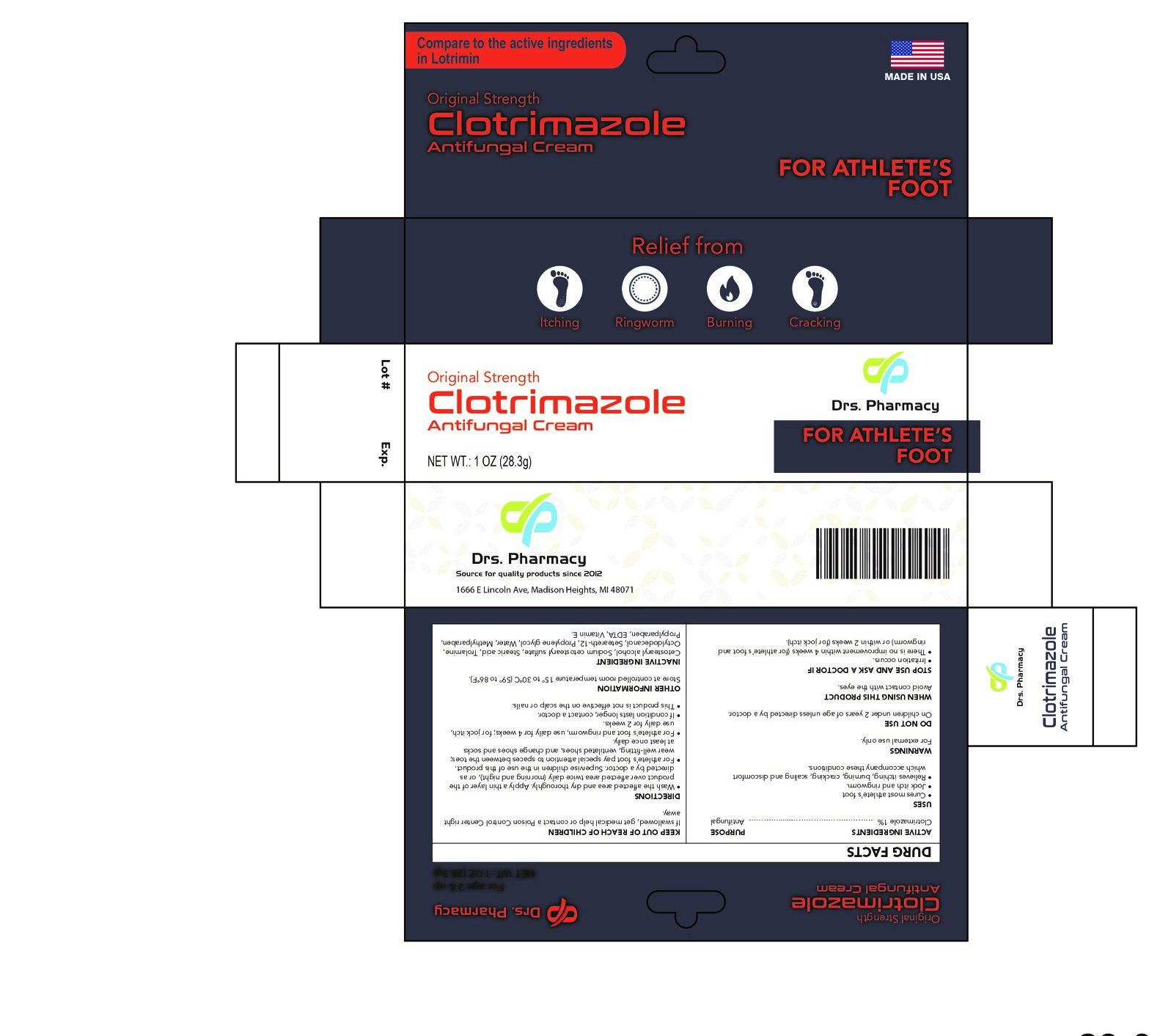 DRUG LABEL: Clotrimazole
NDC: 80489-002 | Form: CREAM
Manufacturer: OL PHARMA TECH,LLC
Category: otc | Type: HUMAN OTC DRUG LABEL
Date: 20250109

ACTIVE INGREDIENTS: CLOTRIMAZOLE 10 mg/1 g
INACTIVE INGREDIENTS: CETOSTEARYL ALCOHOL; PROPYLENE GLYCOL; EDETATE DISODIUM; CETEARETH-12; METHYLPARABEN; STEARIC ACID; .ALPHA.-TOCOPHEROL; MINERAL OIL; SODIUM CETOSTEARYL SULFATE; TROLAMINE; WATER; PROPYLPARABEN

ACTIVE INGREDIENT

Clotrimazole 1%

PURPOSE

Antifungal

USES

- cures most athlete's foot, jock itch and ringworm
- relieves itching, burning, cracking, scaling and discomfort which accompany these conditions

warnings

For external use only

Do not use on children under 2 years of age unless directed by a doctor.

WHEN USING THIS PRODUCT

avoid contact with the eyes

Stop use and ask your doctor if:

- irritation occurs
- there is no improvement within 4 weeks (for athlete's foot and ringworm) or within 2 weeks (for jock itch)

Keep out of reach of children.

If swallowed, get medical help or contact a Poison Control Center right away.

Directions:

- wash the affected area and dry thoroughly
- apply a thin layer of the product over affected area twice daily (morning and night), or as directed by a

doctor

- supervise children in the use of this product
- for athlete's foot: pay special attention to spaces between the toes; wear well-fitting, ventilated shoes,

and change shoes and socks at least once daily

- for athlete's foot and ringworm, use daily for 4 weeks; for jock itch, use daily for 2 weeks

if condition lasts longer, contact a doctor

- this product is not effective on the scalp or nails

Other information

- store at controlled room temperature 59°-86°F (15°-30°C).
- before using any medication, read all label directions. Keep carton, it contains important information

Inactive ingredients

sodium cetostearyl sulfate, cetostearyl alcohol, stearic acid, trolamine, mineral oil , ceteareth-12, propylene glycol, methyl parabeen, propyl paraben, EDTA disodium, vitamin E, water

For Questions:

www.drspharmacyusa.com

PACKAGE LABEL

original strenghth

Antifungal cream